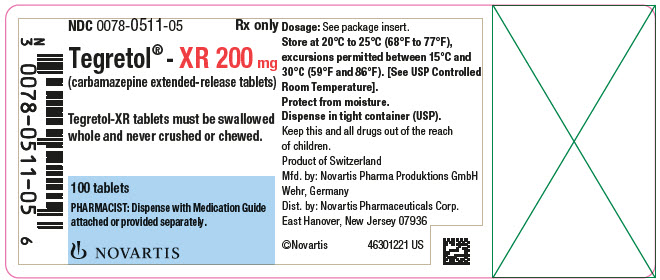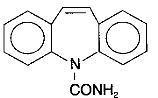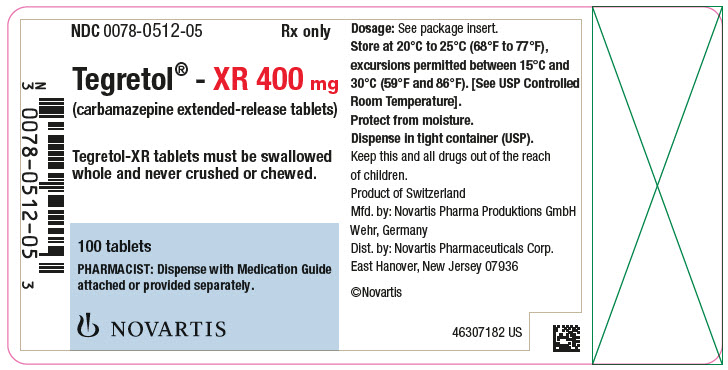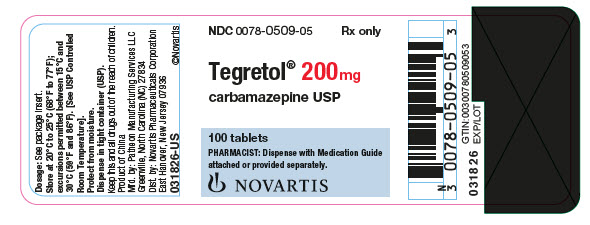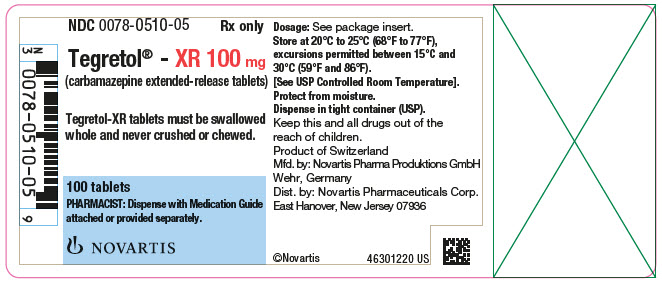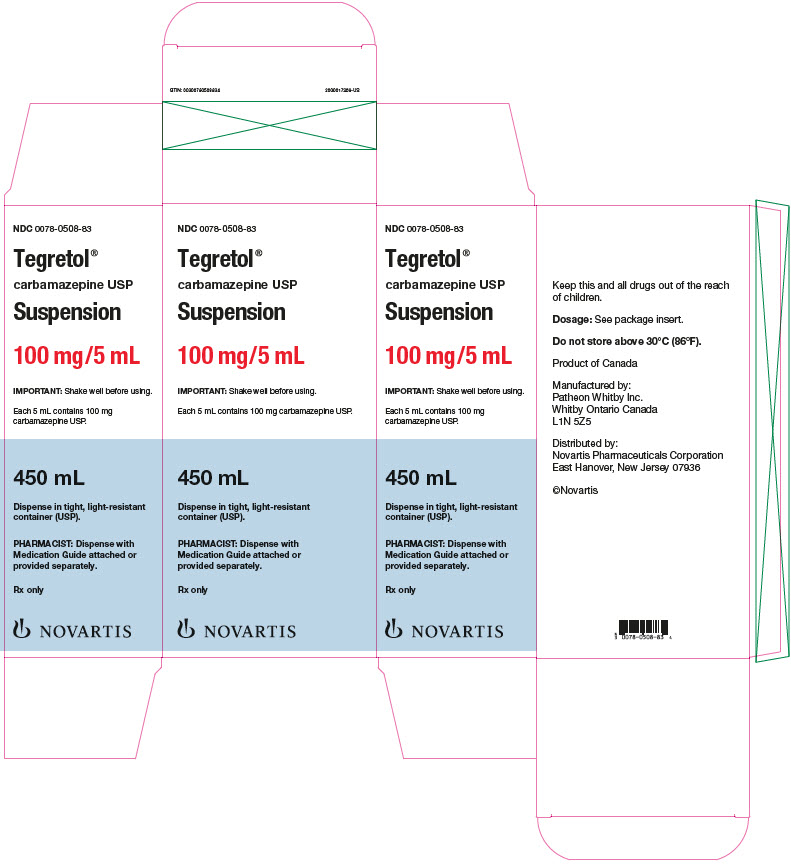 DRUG LABEL: Tegretol
NDC: 0078-0508 | Form: SUSPENSION
Manufacturer: Novartis Pharmaceuticals Corporation
Category: prescription | Type: HUMAN PRESCRIPTION DRUG LABEL
Date: 20251216

ACTIVE INGREDIENTS: CARBAMAZEPINE 100 mg/5 mL
INACTIVE INGREDIENTS: CITRIC ACID MONOHYDRATE; FD&C YELLOW NO. 6; POTASSIUM SORBATE; PROPYLENE GLYCOL; WATER; SORBITOL; SUCROSE; XANTHAN GUM

Tegretol

Tegretol®

carbamazepine USP

Tablets of 200 mg – pink

Suspension of 100 mg/5 mL

Tegretol®-XR

(carbamazepine extended-release tablets)

100 mg, 200 mg, 400 mg

Rx only

Prescribing Information

WARNINGS

SERIOUS DERMATOLOGIC REACTIONS AND HLA-B*1502 ALLELE

SERIOUS AND SOMETIMES FATAL DERMATOLOGIC REACTIONS, INCLUDING TOXIC EPIDERMAL NECROLYSIS (TEN) AND STEVENS-JOHNSON SYNDROME (SJS), HAVE BEEN REPORTED DURING TREATMENT WITH TEGRETOL. THESE REACTIONS ARE ESTIMATED TO OCCUR IN 1 TO 6 PER 10,000 NEW USERS IN COUNTRIES WITH MAINLY CAUCASIAN POPULATIONS, BUT THE RISK IN SOME ASIAN COUNTRIES IS ESTIMATED TO BE ABOUT 10 TIMES HIGHER. STUDIES IN PATIENTS OF CHINESE ANCESTRY HAVE FOUND A STRONG ASSOCIATION BETWEEN THE RISK OF DEVELOPING SJS/TEN AND THE PRESENCE OF HLA-B*1502, AN INHERITED ALLELIC VARIANT OF THE HLA-B GENE. HLA-B*1502 IS FOUND ALMOST EXCLUSIVELY IN PATIENTS WITH ANCESTRY ACROSS BROAD AREAS OF ASIA. PATIENTS WITH ANCESTRY IN GENETICALLY AT-RISK POPULATIONS SHOULD BE SCREENED FOR THE PRESENCE OF HLA-B*1502 PRIOR TO INITIATING TREATMENT WITH TEGRETOL. PATIENTS TESTING POSITIVE FOR THE ALLELE SHOULD NOT BE TREATED WITH TEGRETOL UNLESS THE BENEFIT CLEARLY OUTWEIGHS THE RISK (SEE WARNINGS AND PRECAUTIONS, LABORATORY TESTS).

APLASTIC ANEMIA AND AGRANULOCYTOSIS

APLASTIC ANEMIA AND AGRANULOCYTOSIS HAVE BEEN REPORTED IN ASSOCIATION WITH THE USE OF TEGRETOL. DATA FROM A POPULATION-BASED CASE CONTROL STUDY DEMONSTRATE THAT THE RISK OF DEVELOPING THESE REACTIONS IS 5 TO 8 TIMES GREATER THAN IN THE GENERAL POPULATION. HOWEVER, THE OVERALL RISK OF THESE REACTIONS IN THE UNTREATED GENERAL POPULATION IS LOW, APPROXIMATELY SIX PATIENTS PER ONE MILLION POPULATION PER YEAR FOR AGRANULOCYTOSIS AND TWO PATIENTS PER ONE MILLION POPULATION PER YEAR FOR APLASTIC ANEMIA.

ALTHOUGH REPORTS OF TRANSIENT OR PERSISTENT DECREASED PLATELET OR WHITE BLOOD CELL COUNTS ARE NOT UNCOMMON IN ASSOCIATION WITH THE USE OF TEGRETOL, DATA ARE NOT AVAILABLE TO ESTIMATE ACCURATELY THEIR INCIDENCE OR OUTCOME. HOWEVER, THE VAST MAJORITY OF THE CASES OF LEUKOPENIA HAVE NOT PROGRESSED TO THE MORE SERIOUS CONDITIONS OF APLASTIC ANEMIA OR AGRANULOCYTOSIS.

BECAUSE OF THE VERY LOW INCIDENCE OF AGRANULOCYTOSIS AND APLASTIC ANEMIA, THE VAST MAJORITY OF MINOR HEMATOLOGIC CHANGES OBSERVED IN MONITORING OF PATIENTS ON TEGRETOL ARE UNLIKELY TO SIGNAL THE OCCURRENCE OF EITHER ABNORMALITY. NONETHELESS, COMPLETE PRETREATMENT HEMATOLOGICAL TESTING SHOULD BE OBTAINED AS A BASELINE. IF A PATIENT IN THE COURSE OF TREATMENT EXHIBITS LOW OR DECREASED WHITE BLOOD CELL OR PLATELET COUNTS, THE PATIENT SHOULD BE MONITORED CLOSELY. DISCONTINUATION OF THE DRUG SHOULD BE CONSIDERED IF ANY EVIDENCE OF SIGNIFICANT BONE MARROW DEPRESSION DEVELOPS.

Before prescribing Tegretol, the physician should be thoroughly familiar with the details of this prescribing information, particularly regarding use with other drugs, especially those which accentuate toxicity potential.

DESCRIPTION

Tegretol, carbamazepine USP, is an anticonvulsant and specific analgesic for trigeminal neuralgia, available for oral administration as tablets of 200 mg, XR tablets of 100, 200, and 400 mg, and as a suspension of 100 mg/5 mL (teaspoon). Its chemical name is 5H-dibenz[b,f ]azepine-5-carboxamide, and its structural formula is:

Carbamazepine USP is a white to off-white powder, practically insoluble in water and soluble in alcohol and in acetone. Its molecular weight is 236.27 g/mol.

Inactive Ingredients

Tablets: Colloidal silicon dioxide, FD&C Red No. 40, gelatin, glycerin, magnesium stearate, starch, and stearic acid.

Suspension: Citric acid, FD&C Yellow No. 6, flavoring, polymer, potassium sorbate, propylene glycol, purified water, sorbitol, sucrose, and xanthan gum. The amount of propylene glycol in Tegretol suspension is 25 mg per mL (see WARNINGS Propylene Glycol Toxicity).

Tegretol-XR tablets: cellulose compounds, dextrates, iron oxides, magnesium stearate, mannitol, polyethylene glycol, sodium lauryl sulfate, titanium dioxide (200 mg tablets only).

CLINICAL PHARMACOLOGY

In controlled clinical trials, Tegretol has been shown to be effective in the treatment of psychomotor and grand mal seizures, as well as trigeminal neuralgia.

Mechanism of Action

Tegretol has demonstrated anticonvulsant properties in rats and mice with electrically and chemically induced seizures. It appears to act by reducing polysynaptic responses and blocking the post-tetanic potentiation. Tegretol greatly reduces or abolishes pain induced by stimulation of the infraorbital nerve in cats and rats. It depresses thalamic potential and bulbar and polysynaptic reflexes, including the linguomandibular reflex in cats. Tegretol is chemically unrelated to other anticonvulsants or other drugs used to control the pain of trigeminal neuralgia. The mechanism of action remains unknown.

The principal metabolite of Tegretol, carbamazepine-10,11-epoxide, has anticonvulsant activity as demonstrated in several in vivo animal models of seizures. Though clinical activity for the epoxide has been postulated, the significance of its activity with respect to the safety and efficacy of Tegretol has not been established.

Pharmacokinetics

In clinical studies, Tegretol suspension, conventional tablets, and XR tablets delivered equivalent amounts of drug to the systemic circulation. However, the suspension was absorbed somewhat faster, and the XR tablet slightly slower, than the conventional tablet. The bioavailability of the XR tablet was 89% compared to suspension. Following a twice a day dosage regimen, the suspension provides higher peak levels and lower trough levels than those obtained from the conventional tablet for the same dosage regimen. On the other hand, following a three times a day dosage regimen, Tegretol suspension affords steady-state plasma levels comparable to Tegretol tablets given twice a day when administered at the same total mg daily dose. Following a twice a day dosage regimen, Tegretol-XR tablets afford steady-state plasma levels comparable to conventional Tegretol tablets given four times a day, when administered at the same total mg daily dose. Tegretol in blood is 76% bound to plasma proteins. Plasma levels of Tegretol are variable and may range from 0.5 to 25 mcg/mL, with no apparent relationship to the daily intake of the drug. Usual adult therapeutic levels are between 4 and 12 mcg/mL. In polytherapy, the concentration of Tegretol and concomitant drugs may be increased or decreased during therapy, and drug effects may be altered (see PRECAUTIONS, Drug Interactions). Following chronic oral administration of suspension, plasma levels peak at approximately 1.5 hours compared to 4 to 5 hours after administration of conventional Tegretol tablets, and 3 to 12 hours after administration of Tegretol-XR tablets. The CSF/serum ratio is 0.22, similar to the 24% unbound Tegretol in serum. Because Tegretol induces its own metabolism, the half-life is also variable. Autoinduction is completed after 3 to 5 weeks of a fixed dosing regimen. Initial half-life values range from 25 to 65 hours, decreasing to 12 to 17 hours on repeated doses. Tegretol is metabolized in the liver. Cytochrome P450 3A4 was identified as the major isoform responsible for the formation of carbamazepine-10,11-epoxide from Tegretol. Human microsomal epoxide hydrolase has been identified as the enzyme responsible for the formation of the 10,11-transdiol derivative from carbamazepine-10,11 epoxide. After oral administration of ^14C-carbamazepine, 72% of the administered radioactivity was found in the urine and 28% in the feces. This urinary radioactivity was composed largely of hydroxylated and conjugated metabolites, with only 3% of unchanged Tegretol.

The pharmacokinetic parameters of Tegretol disposition are similar in children and in adults. However, there is a poor correlation between plasma concentrations of carbamazepine and Tegretol dose in children. Carbamazepine is more rapidly metabolized to carbamazepine-10,11-epoxide (a metabolite shown to be equipotent to carbamazepine as an anticonvulsant in animal screens) in the younger age groups than in adults. In children below the age of 15, there is an inverse relationship between CBZ-E/CBZ ratio and increasing age (in one report from 0.44 in children below the age of 1 year to 0.18 in children between 10 to 15 years of age).

The effects of race and gender on carbamazepine pharmacokinetics have not been systematically evaluated.

INDICATIONS AND USAGE

Epilepsy

Tegretol is indicated for use as an anticonvulsant drug. Evidence supporting efficacy of Tegretol as an anticonvulsant was derived from active drug-controlled studies that enrolled patients with the following seizure types:

1. Partial seizures with complex symptomatology (psychomotor, temporal lobe). Patients with these seizures appear to show greater improvement than those with other types.
2. Generalized tonic-clonic seizures (grand mal).
3. Mixed seizure patterns which include the above, or other partial or generalized seizures. Absence seizures (petit mal) do not appear to be controlled by Tegretol (see PRECAUTIONS, General).

Trigeminal Neuralgia

Tegretol is indicated in the treatment of the pain associated with true trigeminal neuralgia.

Beneficial results have also been reported in glossopharyngeal neuralgia.

This drug is not a simple analgesic and should not be used for the relief of trivial aches or pains.

CONTRAINDICATIONS

Tegretol should not be used in patients with a history of previous bone marrow depression, hypersensitivity to the drug, or known sensitivity to any of the tricyclic compounds, such as amitriptyline, desipramine, imipramine, protriptyline, nortriptyline, etc. Likewise, on theoretical grounds its use with monoamine oxidase (MAO) inhibitors is not recommended. Before administration of Tegretol, MAO inhibitors should be discontinued for a minimum of 14 days, or longer if the clinical situation permits.

Coadministration of carbamazepine and nefazodone may result in insufficient plasma concentrations of nefazodone and its active metabolite to achieve a therapeutic effect. Coadministration of carbamazepine with nefazodone is contraindicated.

WARNINGS

Serious Dermatologic Reactions

Serious and sometimes fatal dermatologic reactions, including toxic epidermal necrolysis (TEN) and Stevens-Johnson syndrome (SJS), have been reported with Tegretol treatment. The risk of these events is estimated to be about 1 to 6 per 10,000 new users in countries with mainly Caucasian populations. However, the risk in some Asian countries is estimated to be about 10 times higher. Tegretol should be discontinued at the first sign of a rash, unless the rash is clearly not drug related. If signs or symptoms suggest SJS/TEN, use of this drug should not be resumed, and alternative therapy should be considered.

SJS/TEN and HLA-B*1502 Allele

Retrospective case-control studies have found that in patients of Chinese ancestry there is a strong association between the risk of developing SJS/TEN with carbamazepine treatment and the presence of an inherited variant of the HLA-B gene, HLA-B*1502. The occurrence of higher rates of these reactions in countries with higher frequencies of this allele suggests that the risk may be increased in allele-positive individuals of any ethnicity.

Across Asian populations, notable variation exists in the prevalence of HLA-B*1502. Greater than 15% of the population is reported positive in Hong Kong, Thailand, Malaysia, and parts of the Philippines, compared to about 10% in Taiwan and 4% in North China. South Asians, including Indians, appear to have intermediate prevalence of HLA-B*1502, averaging 2% to 4%, but higher in some groups. HLA-B*1502 is present in less than 1% of the population in Japan and Korea.

HLA-B*1502 is largely absent in individuals not of Asian origin (e.g., Caucasians, African-Americans, Hispanics, and Native Americans).

Prior to initiating Tegretol therapy, testing for HLA-B*1502 should be performed in patients with ancestry in populations in which HLA-B*1502 may be present. In deciding which patients to screen, the rates provided above for the prevalence of HLA-B*1502 may offer a rough guide, keeping in mind the limitations of these figures due to wide variability in rates even within ethnic groups, the difficulty in ascertaining ethnic ancestry, and the likelihood of mixed ancestry. Tegretol should not be used in patients positive for HLA-B*1502 unless the benefits clearly outweigh the risks. Tested patients who are found to be negative for the allele are thought to have a low risk of SJS/TEN (see BOXED WARNING and PRECAUTIONS, Laboratory Tests).

Over 90% of Tegretol treated patients who will experience SJS/TEN have this reaction within the first few months of treatment. This information may be taken into consideration in determining the need for screening of genetically at-risk patients currently on Tegretol.

The HLA-B*1502 allele has not been found to predict risk of less severe adverse cutaneous reactions from Tegretol, such as maculopapular eruption (MPE) or to predict Drug Reaction with Eosinophilia and Systemic Symptoms (DRESS).

Limited evidence suggests that HLA-B*1502 may be a risk factor for the development of SJS/TEN in patients of Chinese ancestry taking other antiepileptic drugs associated with SJS/TEN, including phenytoin. Consideration should be given to avoiding use of other drugs associated with SJS/TEN in HLA-B*1502 positive patients, when alternative therapies are otherwise equally acceptable.

Hypersensitivity Reactions and HLA-A*3101 Allele

Retrospective case-control studies in patients of European, Korean, and Japanese ancestry have found a moderate association between the risk of developing hypersensitivity reactions and the presence of HLA-A*3101, an inherited allelic variant of the HLA-A gene, in patients using carbamazepine. These hypersensitivity reactions include SJS/TEN, maculopapular eruptions, and Drug Reaction with Eosinophilia and Systemic Symptoms (see DRESS/Multiorgan hypersensitivity below).

HLA-A*3101 is expected to be carried by more than 15% of patients of Japanese, Native American, Southern Indian (for example, Tamil Nadu), and some Arabic ancestry; up to about 10% in patients of Han Chinese, Korean, European, Latin American, and other Indian ancestry; and up to about 5% in African-Americans, and patients of Thai, Taiwanese, and Chinese (Hong Kong) ancestry.

The risks and benefits of Tegretol therapy should be weighed before considering Tegretol in patients known to be positive for HLA-A*3101.

Application of HLA genotyping as a screening tool has important limitations and must never substitute for appropriate clinical vigilance and patient management. Many HLA-B*1502-positive and HLA-A*3101-positive patients treated with Tegretol will not develop SJS/TEN or other hypersensitivity reactions, and these reactions can still occur infrequently in HLA-B*1502-negative and HLA-A*3101-negative patients of any ethnicity. The role of other possible factors in the development of, and morbidity from, SJS/TEN and other hypersensitivity reactions, such as antiepileptic drug (AED) dose, compliance, concomitant medications, comorbidities, and the level of dermatologic monitoring, have not been studied.

Aplastic anemia and agranulocytosis have been reported in association with the use of Tegretol (see BOXED WARNING). Patients with a history of adverse hematologic reaction to any drug may be particularly at risk of bone marrow depression.

Drug Reaction with Eosinophilia and Systemic Symptoms (DRESS)/Multiorgan Hypersensitivity

Drug Reaction with Eosinophilia and Systemic Symptoms (DRESS), also known as multiorgan hypersensitivity, has occurred with Tegretol. Some of these events have been fatal or life-threatening. DRESS typically, although not exclusively, presents with fever, rash, lymphadenopathy, and/or facial swelling, in association with other organ system involvement, such as hepatitis, nephritis, hematologic abnormalities, myocarditis, or myositis sometimes resembling an acute viral infection. Eosinophilia is often present. This disorder is variable in its expression, and other organ systems not noted here may be involved. It is important to note that early manifestations of hypersensitivity (e.g., fever, lymphadenopathy) may be present even though rash is not evident. If such signs or symptoms are present, the patient should be evaluated immediately. Tegretol should be discontinued if an alternative etiology for the signs or symptoms cannot be established.

Hypersensitivity

Hypersensitivity reactions to carbamazepine have been reported in patients who previously experienced this reaction to anticonvulsants, including phenytoin, primidone, and phenobarbital. If such history is present, benefits and risks should be carefully considered and, if carbamazepine is initiated, the signs and symptoms of hypersensitivity should be carefully monitored.

Patients should be informed that about a third of patients who have had hypersensitivity reactions to carbamazepine also experience hypersensitivity reactions with oxcarbazepine (Trileptal®).

Anaphylaxis and Angioedema

Rare cases of anaphylaxis and angioedema involving the larynx, glottis, lips, and eyelids have been reported in patients after taking the first or subsequent doses of Tegretol. Angioedema associated with laryngeal edema can be fatal. If a patient develops any of these reactions after treatment with Tegretol, the drug should be discontinued and an alternative treatment started. These patients should not be rechallenged with the drug.

Propylene Glycol Toxicity

Tegretol suspension contains propylene glycol (see DESCRIPTION). Patients less than 5 years of age are at highest risk for propylene glycol toxicity, and a safe level for propylene glycol exposure with repeated administration has not been established for this age group. Particularly, neonates i.e., less than 4 weeks of age (including full-term babies and pre-term babies less than 44 post-menstrual weeks of age) are known to have immature metabolic and renal clearance of propylene glycol. Therefore, Tegretol suspension should only be used in neonates after careful risk-benefit assessment if no therapeutic alternatives are available. When Tegretol suspension is administered at the maximum dose (35 mg/kg/day) for treatment of epilepsy, the exposure to propylene glycol will be 44 mg/kg/day. The total daily intake of propylene glycol from all sources, including concomitant drugs, should be considered in managing the risk of propylene glycol toxicity.

Monitor patients for signs of potential propylene glycol toxicity, including hemolysis, hyperosmolarity with anion gap metabolic acidosis, acute kidney injury, and central nervous system (CNS) toxicity. Discontinue Tegretol suspension if propylene glycol toxicity is suspected (see DESCRIPTION).

Suicidal Behavior and Ideation

Antiepileptic drugs (AEDs), including Tegretol, increase the risk of suicidal thoughts or behavior in patients taking these drugs for any indication. Patients treated with any AED for any indication should be monitored for the emergence or worsening of depression, suicidal thoughts or behavior, and/or any unusual changes in mood or behavior.

Pooled analyses of 199 placebo-controlled clinical trials (mono- and adjunctive therapy) of 11 different AEDs showed that patients randomized to one of the AEDs had approximately twice the risk (adjusted Relative Risk 1.8, 95% CI:1.2, 2.7) of suicidal thinking or behavior compared to patients randomized to placebo. In these trials, which had a median treatment duration of 12 weeks, the estimated incidence rate of suicidal behavior or ideation among 27,863 AED-treated patients was 0.43%, compared to 0.24% among 16,029 placebo-treated patients, representing an increase of approximately one case of suicidal thinking or behavior for every 530 patients treated. There were four suicides in drug-treated patients in the trials and none in placebo-treated patients, but the number is too small to allow any conclusion about drug effect on suicide.

The increased risk of suicidal thoughts or behavior with AEDs was observed as early as one week after starting drug treatment with AEDs and persisted for the duration of treatment assessed. Because most trials included in the analysis did not extend beyond 24 weeks, the risk of suicidal thoughts or behavior beyond 24 weeks could not be assessed.

The risk of suicidal thoughts or behavior was generally consistent among drugs in the data analyzed. The finding of increased risk with AEDs of varying mechanisms of action and across a range of indications suggests that the risk applies to all AEDs used for any indication. The risk did not vary substantially by age (5 to 100 years) in the clinical trials analyzed. Table 1 shows absolute and relative risk by indication for all evaluated AEDs.

Table 1. Risk by Indication for Antiepileptic Drugs in the Pooled Analysis
Indication | Placebo patients with events per 1,000 patients | Drug patients with events per 1,000 patients | Relative risk: incidence of events in drug patients/incidence in placebo patients | Risk difference: additional drug patients with events per 1,000 patients
Epilepsy | 1.0 | 3.4 | 3.5 | 2.4
Psychiatric | 5.7 | 8.5 | 1.5 | 2.9
Other | 1.0 | 1.8 | 1.9 | 0.9
Total | 2.4 | 4.3 | 1.8 | 1.9

The relative risk for suicidal thoughts or behavior was higher in clinical trials for epilepsy than in clinical trials for psychiatric or other conditions, but the absolute risk differences were similar for the epilepsy and psychiatric indications.

Anyone considering prescribing Tegretol, or any other AED must balance the risk of suicidal thoughts or behavior with the risk of untreated illness. Epilepsy and many other illnesses for which AEDs are prescribed are themselves associated with morbidity and mortality and an increased risk of suicidal thoughts and behavior. Should suicidal thoughts and behavior emerge during treatment, the prescriber needs to consider whether the emergence of these symptoms in any given patient may be related to the illness being treated.

General

Tegretol has shown mild anticholinergic activity that may be associated with increased intraocular pressure; therefore, patients with increased intraocular pressure should be closely observed during therapy.

Because of the relationship of the drug to other tricyclic compounds, the possibility of activation of a latent psychosis and, in elderly patients, of confusion or agitation should be borne in mind.

The use of Tegretol should be avoided in patients with a history of hepatic porphyria (e.g., acute intermittent porphyria, variegate porphyria, porphyria cutanea tarda). Acute attacks have been reported in such patients receiving Tegretol therapy. Carbamazepine administration has also been demonstrated to increase porphyrin precursors in rodents, a presumed mechanism for the induction of acute attacks of porphyria.

As with all antiepileptic drugs, Tegretol should be withdrawn gradually to minimize the potential of increased seizure frequency.

Hyponatremia can occur as a result of treatment with Tegretol. In many cases, the hyponatremia appears to be caused by the syndrome of inappropriate antidiuretic hormone secretion (SIADH). The risk of developing SIADH with Tegretol treatment appears to be dose-related. Elderly patients and patients treated with diuretics are at greater risk of developing hyponatremia. Signs and symptoms of hyponatremia include headache, new or increased seizure frequency, difficulty concentrating, memory impairment, confusion, weakness, and unsteadiness, which can lead to falls. Consider discontinuing Tegretol in patients with symptomatic hyponatremia.

Usage in Pregnancy

Carbamazepine can cause fetal harm when administered to a pregnant woman.

Epidemiological data suggest that there may be an association between the use of carbamazepine during pregnancy and congenital malformations, including spina bifida. There have also been reports that associate carbamazepine with developmental disorders and congenital anomalies (e.g., craniofacial defects, cardiovascular malformations, and anomalies involving various body systems). Developmental delays based on neurobehavioral assessments have been reported. When treating or counseling women of childbearing potential, the prescribing physician will wish to weigh the benefits of therapy against the risks. If this drug is used during pregnancy, or if the patient becomes pregnant while taking this drug, the patient should be apprised of the potential hazard to the fetus.

Retrospective case reviews suggest that, compared with monotherapy, there may be a higher prevalence of teratogenic effects associated with the use of anticonvulsants in combination therapy. Therefore, if therapy is to be continued, monotherapy may be preferable for pregnant women.

In humans, transplacental passage of carbamazepine is rapid (30 to 60 minutes), and the drug is accumulated in the fetal tissues, with higher levels found in liver and kidney than in brain and lung.

Carbamazepine has been shown to have adverse effects in reproduction studies in rats when given orally in dosages 10 to 25 times the maximum human daily dosage (MHDD) of 1200 mg on a mg/kg basis or 1.5 to 4 times the MHDD on a mg/m^2 basis. In rat teratology studies, 2 of 135 offspring showed kinked ribs at 250 mg/kg and 4 of 119 offspring at 650 mg/kg showed other anomalies (cleft palate, 1; talipes, 1; anophthalmos, 2). In reproduction studies in rats, nursing offspring demonstrated a lack of weight gain and an unkempt appearance at a maternal dosage level of 200 mg/kg.

There have been a few cases of neonatal seizures and/or respiratory depression associated with maternal Tegretol and other concomitant anticonvulsant drug use. A few cases of neonatal vomiting, diarrhea, and/or decreased feeding have also been reported in association with maternal Tegretol use. These symptoms may represent a neonatal withdrawal syndrome.

To provide information regarding the effects of in utero exposure to Tegretol, physicians are advised to recommend that pregnant patients taking Tegretol enroll in the North American Antiepileptic Drug (NAAED) Pregnancy Registry. This can be done by calling the toll-free number 1-888-233-2334 and must be done by patients themselves. Information on the registry can also be found at the website http://www.aedpregnancyregistry.org/.

Clinical Considerations

Disease-associated Maternal and/or Embryofetal Risk

Epilepsy, with or without exposure to antiepileptic drugs, has been associated with several adverse outcomes during pregnancy, including preeclampsia, preterm labor, antepartum and postpartum hemorrhage, placental abruption, poor fetal growth, prematurity, fetal death, and maternal mortality. The risk of maternal or fetal injury may be greatest for patients with untreated or poorly controlled convulsive seizures.

Women with epilepsy who become pregnant should not abruptly discontinue antiepileptic drugs, including TEGRETOL, due to the risk of status epilepticus or severe seizures, which may be life-threatening.

PRECAUTIONS

General

Before initiating therapy, a detailed history and physical examination should be made.

Tegretol should be used with caution in patients with a mixed seizure disorder that includes atypical absence seizures, since in these patients Tegretol has been associated with increased frequency of generalized convulsions (see INDICATIONS AND USAGE).

Therapy should be prescribed only after critical benefit-to-risk appraisal in patients with a history of cardiac conduction disturbance, including second- and third-degree AV heart block; cardiac, hepatic, or renal damage; adverse hematologic or hypersensitivity reaction to other drugs, including reactions to other anticonvulsants; or interrupted courses of therapy with Tegretol.

AV heart block, including second- and third-degree block, have been reported following Tegretol treatment. This occurred generally, but not solely, in patients with underlying EKG abnormalities or risk factors for conduction disturbances.

Hepatic effects, ranging from slight elevations in liver enzymes to rare cases of hepatic failure have been reported (see ADVERSE REACTIONS and PRECAUTIONS, Laboratory Tests). In some cases, hepatic effects may progress despite discontinuation of the drug. In addition, rare instances of vanishing bile duct syndrome have been reported. This syndrome consists of a cholestatic process with a variable clinical course ranging from fulminant to indolent, involving the destruction and disappearance of the intrahepatic bile ducts. Some, but not all, cases are associated with features that overlap with other immunoallergenic syndromes, such as multiorgan hypersensitivity (DRESS syndrome) and serious dermatologic reactions. As an example, there has been a report of vanishing bile duct syndrome associated with SJS and in another case an association with fever and eosinophilia.

Since a given dose of Tegretol suspension will produce higher peak levels than the same dose given as the tablet, it is recommended that patients given the suspension be started on lower doses and increased slowly to avoid unwanted side effects (see DOSAGE AND ADMINISTRATION).

Tegretol suspension contains sorbitol and, therefore, should not be administered to patients with rare hereditary problems of fructose intolerance.

Information for Patients

Patients should be informed of the availability of a Medication Guide, and they should be instructed to read the Medication Guide before taking Tegretol.

Patients should be made aware of the early toxic signs and symptoms of a potential hematologic problem, as well as dermatologic, hypersensitivity or hepatic reactions. These symptoms may include, but are not limited to, fever, sore throat, rash, ulcers in the mouth, easy bruising, lymphadenopathy and petechial or purpuric hemorrhage, and in the case of liver reactions, anorexia, nausea/vomiting, or jaundice. The patient should be advised that, because these signs and symptoms may signal a serious reaction, that they must report any occurrence immediately to a physician. In addition, the patient should be advised that these signs and symptoms should be reported even if mild or when occurring after extended use.

Patients should be advised that serious skin reactions have been reported in association with Tegretol. In the event a skin reaction should occur while taking Tegretol, patients should consult with their physician immediately (see WARNINGS).

Patients should be advised that anaphylactic reactions and angioedema may occur during treatment with Tegretol (see WARNINGS). Advise patients to immediately report signs and symptoms suggesting angioedema (swelling of the face, eyes, lips, or tongue, or difficulty in swallowing or breathing) and to stop taking the drug until they have consulted with their healthcare provider.

Patients, their caregivers, and families should be counseled that AEDs, including Tegretol, may increase the risk of suicidal thoughts and behavior and should be advised of the need to be alert for the emergence or worsening of symptoms of depression, any unusual changes in mood or behavior, or the emergence of suicidal thoughts, behavior, or thoughts about self-harm. Behaviors of concern should be reported immediately to healthcare providers.

Tegretol may interact with some drugs. Therefore, patients should be advised to report to their doctors the use of any other prescription or nonprescription medications or herbal products.

Caution should be exercised if alcohol is taken in combination with Tegretol therapy, due to a possible additive sedative effect.

Since dizziness and drowsiness may occur, patients should be cautioned about the hazards of operating machinery or automobiles or engaging in other potentially dangerous tasks.

Patients should be encouraged to enroll in the NAAED Pregnancy Registry if they become pregnant. This registry is collecting information about the safety of antiepileptic drugs during pregnancy. To enroll, patients can call the toll-free number 1-888-233-2334 (see WARNINGS, Usage in Pregnancy subsection).

Laboratory Tests

For genetically at-risk patients (see WARNINGS), high-resolution ‘HLA-B*1502 typing’ is recommended. The test is positive if either one or two HLA-B*1502 alleles are detected and negative if no HLA-B*1502 alleles are detected.

Complete pretreatment blood counts, including platelets and possibly reticulocytes and serum iron, should be obtained as a baseline. If a patient in the course of treatment exhibits low or decreased white blood cell or platelet counts, the patient should be monitored closely. Discontinuation of the drug should be considered if any evidence of significant bone marrow depression develops.

Baseline and periodic evaluations of liver function, particularly in patients with a history of liver disease, must be performed during treatment with this drug since liver damage may occur (see PRECAUTIONS, General and ADVERSE REACTIONS). Carbamazepine should be discontinued, based on clinical judgment, if indicated by newly occurring or worsening clinical or laboratory evidence of liver dysfunction or hepatic damage, or in the case of active liver disease.

Baseline and periodic eye examinations, including slit-lamp, funduscopy, and tonometry, are recommended since many phenothiazines and related drugs have been shown to cause eye changes.

Baseline and periodic complete urinalysis and BUN determinations are recommended for patients treated with this agent because of observed renal dysfunction.

Monitoring of blood levels (see CLINICAL PHARMACOLOGY) has increased the efficacy and safety of anticonvulsants. This monitoring may be particularly useful in cases of dramatic increase in seizure frequency and for verification of compliance. In addition, measurement of drug serum levels may aid in determining the cause of toxicity when more than one medication is being used.

Thyroid function tests have been reported to show decreased values with Tegretol administered alone.

Interference with some pregnancy tests has been reported.

Drug Interactions

There has been a report of a patient who passed an orange rubbery precipitate in his stool the day after ingesting Tegretol suspension immediately followed by Thorazine®* solution. Subsequent testing has shown that mixing Tegretol suspension and chlorpromazine solution (both generic and brand name) as well as Tegretol suspension and liquid Mellaril®, resulted in the occurrence of this precipitate. Because the extent to which this occurs with other liquid medications is not known, Tegretol suspension should not be administered simultaneously with other liquid medicinal agents or diluents (see DOSAGE AND ADMINISTRATION).

Clinically meaningful drug interactions have occurred with concomitant medications and include (but are not limited to) the following:

Agents That May Affect Tegretol Plasma Levels

When carbamazepine is given with drugs that can increase or decrease carbamazepine levels, close monitoring of carbamazepine levels is indicated and dosage adjustment may be required.

Agents That Increase Carbamazepine Levels

CYP3A4 inhibitors inhibit Tegretol metabolism and can thus increase plasma carbamazepine levels. Drugs that have been shown, or would be expected, to increase plasma carbamazepine levels include aprepitant, cimetidine, ciprofloxacin, danazol, diltiazem, macrolides (e.g., erythromycin, clarithromycin), fluoxetine, fluvoxamine, trazodone, omeprazole, oxybutynin, isoniazid, niacinamide (nicotinamide), azoles (e.g., ketaconazole, itraconazole, fluconazole, voriconazole), acetazolamide, verapamil, ticlopidine, grapefruit juice, and protease inhibitors.

Human microsomal epoxide hydrolase has been identified as the enzyme responsible for the formation of the 10,11-transdiol derivative from carbamazepine-10,11 epoxide. Coadministration of inhibitors of human microsomal epoxide hydrolase may result in increased carbamazepine-10,11 epoxide plasma concentrations. Accordingly, the dosage of Tegretol should be adjusted and/or the plasma levels monitored when used concomitantly with loxapine, quetiapine, valproic acid, or brivaracetam.

Agents That Decrease Carbamazepine Levels

CYP3A4 inducers can increase the rate of Tegretol metabolism. Drugs that have been shown, or that would be expected, to decrease plasma carbamazepine levels include cisplatin, doxorubicin HCl, felbamate, fosphenytoin, rifampin, phenobarbital, phenytoin, primidone, methsuximide, theophylline, aminophylline.

Effect of Tegretol on Plasma Levels of Concomitant Agents

Decreased Levels of Concomitant Medications

Tegretol is a potent inducer of hepatic 3A4 and is also known to be an inducer of CYP1A2, 2B6, 2C8/9/19, and may therefore reduce plasma concentrations of co-medications mainly metabolized by CYP1A2, 2B6, 2C8/9/19, and 3A4, through induction of their metabolism. When used concomitantly with Tegretol, monitoring of concentrations or dosage adjustment of these agents may be necessary:

- When carbamazepine is added to aripiprazole, the aripiprazole dose should be doubled. Additional dose increases should be based on clinical evaluation. If carbamazepine is later withdrawn, the aripiprazole dose should be reduced.
- When carbamazepine is used with tacrolimus, monitoring of tacrolimus blood concentrations and appropriate dosage adjustments are recommended.
- The use of concomitant strong CYP3A4 inducers, such as carbamazepine should be avoided with temsirolimus. If patients must be coadministered carbamazepine with temsirolimus, an adjustment of temsirolimus dosage should be considered.
- The use of carbamazepine with lapatinib should generally be avoided. If carbamazepine is started in a patient already taking lapatinib, the dose of lapatinib should be gradually titrated up. If carbamazepine is discontinued, the lapatinib dose should be reduced.
- Concomitant use of carbamazepine with nefazodone results in plasma concentrations of nefazodone and its active metabolite insufficient to achieve a therapeutic effect. Coadministration of carbamazepine with nefazodone is contraindicated (see CONTRAINDICATIONS).
- Monitor concentrations of valproate when Tegretol is introduced or withdrawn in patients using valproic acid.

In addition, Tegretol causes, or would be expected to cause, decreased levels of the following drugs, for which monitoring of concentrations or dosage adjustment may be necessary: acetaminophen, albendazole, alprazolam, aprepitant, buprenorphone, bupropion, citalopram, clonazepam, clozapine, corticosteroids (e.g., prednisolone, dexamethasone), cyclosporine, dicumarol, dihydropyridine calcium channel blockers (e.g., felodipine), doxycycline, eslicarbazepine, ethosuximide, everolimus, haloperidol, imatinib, itraconazole, lamotrigine, levothyroxine, methadone, methsuximide, mianserin, midazolam, olanzapine, oral and other hormonal contraceptives, oxcarbazepine, paliperidone, phensuximide, phenytoin, praziquantel, protease inhibitors, risperidone, sertraline, sirolimus, tadalafil, theophylline, tiagabine, topiramate, tramadol, trazodone, tricyclic antidepressants (e.g., imipramine, amitriptyline, nortriptyline), valproate, warfarin, ziprasidone, zonisamide.

Other Drug Interactions

- Cyclophosphamide is an inactive prodrug and is converted to its active metabolite in part by CYP3A. The rate of metabolism and the leukopenic activity of cyclophosphamide are reportedly increased by chronic coadministration of CYP3A4 inducers. There is a potential for increased cyclophosphamide toxicity when coadministered with carbamazepine.
- Concomitant administration of carbamazepine and lithium may increase the risk of neurotoxic side effects.
- Concomitant use of carbamazepine with olanzapine, dantrolene, or ibuprofen may increase plasma carbamazepine levels.
- Concomitant use of carbamazepine and isoniazid has been reported to increase isoniazid-induced hepatotoxicity.
- Alterations of thyroid function have been reported in combination therapy with other anticonvulsant medications.
- Concomitant use of Tegretol with hormonal contraceptive products (e.g., oral, and levonorgestrel subdermal implant contraceptives) may render the contraceptives less effective because the plasma concentrations of the hormones may be decreased. Breakthrough bleeding and unintended pregnancies have been reported. Alternative or back-up methods of contraception should be considered.
- Resistance to the neuromuscular blocking action of the nondepolarizing neuromuscular blocking agents pancuronium, vecuronium, rocuronium and cisatracurium has occurred in patients chronically administered carbamazepine. Whether or not carbamazepine has the same effect on other non-depolarizing agents is unknown. Patients should be monitored closely for more rapid recovery from neuromuscular blockade than expected, and infusion rate requirements may be higher.
- Concomitant use of carbamazepine with rivaroxaban, apixaban, dabigatran, and edoxaban (direct acting oral anticoagulants) is expected to result in decreased plasma concentrations of these anticoagulants that may be insufficient to achieve the intended therapeutic effect. In general, coadministration of carbamazepine with rivaroxaban, apixaban, dabigatran, and edoxaban should be avoided.

Carcinogenesis, Mutagenesis, Impairment of Fertility

Carbamazepine, when administered to Sprague-Dawley rats for two years in the diet at doses of 25, 75, and 250 mg/kg/day, resulted in a dose-related increase in the incidence of hepatocellular tumors in females and of benign interstitial cell adenomas in the testes of males.

Carbamazepine must, therefore, be considered to be carcinogenic in Sprague-Dawley rats. Bacterial and mammalian mutagenicity studies using carbamazepine produced negative results. The significance of these findings relative to the use of carbamazepine in humans is, at present, unknown.

Usage in Pregnancy

(see WARNINGS).

Labor and Delivery

The effect of Tegretol on human labor and delivery is unknown.

Nursing Mothers

Tegretol and its epoxide metabolite are transferred to breast milk. The ratio of the concentration in breast milk to that in maternal plasma is about 0.4 for Tegretol and about 0.5 for the epoxide. The estimated doses given to the newborn during breastfeeding are in the range of 2 to 5 mg daily for Tegretol and 1 to 2 mg daily for the epoxide.

Because of the potential for serious adverse reactions in nursing infants from carbamazepine, a decision should be made whether to discontinue nursing or to discontinue the drug, taking into account the importance of the drug to the mother.

Pediatric Use

Substantial evidence of Tegretol’s effectiveness for use in the management of children with epilepsy (see INDICATIONS AND USAGE for specific seizure types) is derived from clinical investigations performed in adults and from studies in several in vitro systems which support the conclusion that (1) the pathogenetic mechanisms underlying seizure propagation are essentially identical in adults and children, and (2) the mechanism of action of carbamazepine in treating seizures is essentially identical in adults and children.

Taken as a whole, this information supports a conclusion that the generally accepted therapeutic range of total carbamazepine in plasma (i.e., 4 to 12 mcg/mL) is the same in children and adults.

The evidence assembled was primarily obtained from short-term use of carbamazepine. The safety of carbamazepine in children has been systematically studied up to 6 months. No longer-term data from clinical trials is available.

Tegretol suspension contains propylene glycol as an inactive ingredient. Patients less than 5 years of age are at the highest risk for propylene glycol toxicity due to incomplete alcohol dehydrogenase maturity. Particularly, neonates (including full-term babies and pre-term babies less than 44 post-menstrual weeks of age). The total daily intake of propylene glycol from all sources, including concomitant drugs, should be considered in managing the risk of propylene glycol toxicity (see WARNINGS Propylene Glycol Toxicity).

Geriatric Use

No systematic studies in geriatric patients have been conducted.

ADVERSE REACTIONS

If adverse reactions are of such severity that the drug must be discontinued, the physician must be aware that abrupt discontinuation of any anticonvulsant drug in a responsive epileptic patient may lead to seizures or even status epilepticus with its life-threatening hazards.

The most severe adverse reactions have been observed in the hemopoietic system and skin (see BOXED WARNING), the liver, and the cardiovascular system.

The most frequently observed adverse reactions, particularly during the initial phases of therapy, are dizziness, drowsiness, unsteadiness, nausea, and vomiting. To minimize the possibility of such reactions, therapy should be initiated at the lowest dosage recommended.

The following additional adverse reactions have been reported:

Hemopoietic System: Aplastic anemia, agranulocytosis, pancytopenia, bone marrow depression, thrombocytopenia, leukopenia, leukocytosis, eosinophilia, acute intermittent porphyria, variegate porphyria, porphyria cutanea tarda.

Skin: TEN and SJS (see BOXED WARNING), Acute Generalized Exanthematous Pustulosis (AGEP), pruritic and erythematous rashes, urticaria, photosensitivity reactions, alterations in skin pigmentation, exfoliative dermatitis, erythema multiforme and nodosum, purpura, aggravation of disseminated lupus erythematosus, alopecia, diaphoresis, onychomadesis and hirsutism. In certain cases, discontinuation of therapy may be necessary.

Cardiovascular System: Congestive heart failure, edema, aggravation of hypertension, hypotension, syncope and collapse, aggravation of coronary artery disease, arrhythmias and AV block, thrombophlebitis, thromboembolism (e.g., pulmonary embolism), and adenopathy or lymphadenopathy.

Some of these cardiovascular complications have resulted in fatalities. Myocardial infarction has been associated with other tricyclic compounds.

Liver: Abnormalities in liver function tests, cholestatic and hepatocellular jaundice, hepatitis, very rare cases of hepatic failure.

Pancreatic: Pancreatitis.

Respiratory System: Pulmonary hypersensitivity characterized by fever, dyspnea, pneumonitis, or pneumonia.

Genitourinary System: Urinary frequency, acute urinary retention, oliguria with elevated blood pressure, azotemia, renal failure, and impotence. Albuminuria, glycosuria, elevated BUN, and microscopic deposits in the urine have also been reported. There have been rare reports of impaired male fertility and/or abnormal spermatogenesis.

Testicular atrophy occurred in rats receiving Tegretol orally from 4 to 52 weeks at dosage levels of 50 to 400 mg/kg/day. Additionally, rats receiving Tegretol in the diet for 2 years at dosage levels of 25, 75, and 250 mg/kg/day had a dose-related incidence of testicular atrophy and aspermatogenesis. In dogs, it produced a brownish discoloration, presumably a metabolite, in the urinary bladder at dosage levels of 50 mg/kg and higher. Relevance of these findings to humans is unknown.

Nervous System: Dizziness, drowsiness, disturbances of coordination, confusion, headache, fatigue, blurred vision, visual hallucinations, transient diplopia, oculomotor disturbances, nystagmus, speech disturbances, abnormal involuntary movements, peripheral neuritis and paresthesias, depression with agitation, talkativeness, tinnitus, hyperacusis, neuroleptic malignant syndrome.

There have been reports of associated paralysis and other symptoms of cerebral arterial insufficiency, but the exact relationship of these reactions to the drug has not been established.

Isolated cases of neuroleptic malignant syndrome have been reported both with and without concomitant use of psychotropic drugs.

Digestive System: Nausea, vomiting, gastric distress and abdominal pain, diarrhea, constipation, anorexia, and dryness of the mouth and pharynx, including glossitis and stomatitis.

Eyes: Scattered punctate cortical lens opacities, increased intraocular pressure (see WARNINGS, General) as well as conjunctivitis, have been reported. Although a direct causal relationship has not been established, many phenothiazines and related drugs have been shown to cause eye changes.

Musculoskeletal System: Aching joints and muscles, and leg cramps.

Metabolism: Fever and chills. Hyponatremia (see WARNINGS, General). Decreased levels of plasma calcium have been reported. Osteoporosis has been reported.

Isolated cases of a lupus erythematosus-like syndrome have been reported. There have been occasional reports of elevated levels of cholesterol, HDL cholesterol, and triglycerides in patients taking anticonvulsants.

A case of aseptic meningitis, accompanied by myoclonus and peripheral eosinophilia, has been reported in a patient taking carbamazepine in combination with other medications. The patient was successfully dechallenged, and the meningitis reappeared upon rechallenge with carbamazepine.

DRUG ABUSE AND DEPENDENCE

No evidence of abuse potential has been associated with Tegretol, nor is there evidence of psychological or physical dependence in humans.

OVERDOSAGE

Acute Toxicity

Lowest known lethal dose: adults, 3.2 g (a 24-year-old woman died of a cardiac arrest and a 24-year-old man died of pneumonia and hypoxic encephalopathy); children, 4 g (a 14-year-old girl died of a cardiac arrest), 1.6 g (a 3-year-old girl died of aspiration pneumonia).

Oral LD50 in animals (mg/kg): mice, 1100 to 3750; rats, 3850 to 4025; rabbits, 1500 to 2680; guinea pigs, 920.

Signs and Symptoms

The first signs and symptoms appear after 1 to 3 hours. Neuromuscular disturbances are the most prominent. Cardiovascular disorders are generally milder, and severe cardiac complications occur only when very high doses (greater than 60 g) have been ingested.

Respiration: Irregular breathing, respiratory depression.

Cardiovascular System: Tachycardia, hypotension or hypertension, shock, conduction disorders.

Nervous System and Muscles: Impairment of consciousness ranging in severity to deep coma. Convulsions, especially in small children. Motor restlessness, muscular twitching, tremor, athetoid movements, opisthotonos, ataxia, drowsiness, dizziness, mydriasis, nystagmus, adiadochokinesia, ballism, psychomotor disturbances, dysmetria. Initial hyperreflexia, followed by hyporeflexia.

Gastrointestinal Tract: Nausea, vomiting.

Kidneys and Bladder: Anuria or oliguria, urinary retention.

Laboratory Findings: Isolated instances of overdosage have included leukocytosis, reduced leukocyte count, glycosuria, and acetonuria. EEG may show dysrhythmias.

Combined Poisoning: When alcohol, tricyclic antidepressants, barbiturates, or hydantoins are taken at the same time, the signs and symptoms of acute poisoning with Tegretol may be aggravated or modified.

Propylene Glycol Toxicity: In cases of suspected overdose with Tegretol suspension, which contains 25 mg of propylene glycol per mL, monitor for signs of propylene glycol toxicity, including hemolysis, hyperosmolarity with anion gap metabolic acidosis, acute kidney injury, CNS toxicity, and multi-organ failure.

Treatment

The prognosis in cases of severe poisoning is critically dependent upon prompt elimination of the drug, which may be achieved by inducing vomiting, irrigating the stomach, and by taking appropriate steps to diminish absorption. If these measures cannot be implemented without risk on the spot, the patient should be transferred at once to a hospital, while ensuring that vital functions are safeguarded. There is no specific antidote.

Elimination of the Drug: Induction of vomiting.

Gastric lavage. Even when more than 4 hours have elapsed following ingestion of the drug, the stomach should be repeatedly irrigated, especially if the patient has also consumed alcohol.

Measures to Reduce Absorption: Activated charcoal, laxatives.

Measures to Accelerate Elimination: Forced diuresis.

Dialysis is indicated only in severe poisoning associated with renal failure. Replacement transfusion is indicated in severe poisoning in small children.

Respiratory Depression: Keep the airways free; resort, if necessary, to endotracheal intubation, artificial respiration, and administration of oxygen.

Hypotension, Shock: Keep the patient’s legs raised and administer a plasma expander. If blood pressure fails to rise despite measures taken to increase plasma volume, use of vasoactive substances should be considered.

Convulsions: Diazepam or barbiturates.

Warning: Diazepam or barbiturates may aggravate respiratory depression (especially in children), hypotension, and coma. However, barbiturates should not be used if drugs that inhibit monoamine oxidase have also been taken by the patient either in overdosage or in recent therapy (within 1 week).

Surveillance: Respiration, cardiac function (ECG monitoring), blood pressure, body temperature, pupillary reflexes, and kidney and bladder function should be monitored for several days.

Treatment of Blood Count Abnormalities: If evidence of significant bone marrow depression develops, the following recommendations are suggested: (1) stop the drug, (2) perform daily CBC, platelet, and reticulocyte counts, (3) do a bone marrow aspiration and trephine biopsy immediately and repeat with sufficient frequency to monitor recovery.

Special periodic studies might be helpful as follows: (1) white cell and platelet antibodies, (2) ^59Fe-ferrokinetic studies, (3) peripheral blood cell typing, (4) cytogenetic studies on marrow and peripheral blood, (5) bone marrow culture studies for colony-forming units, (6) hemoglobin electrophoresis for A2 and F hemoglobin, and (7) serum folic acid and B12 levels.

A fully developed aplastic anemia will require appropriate, intensive monitoring and therapy, for which specialized consultation should be sought.

DOSAGE AND ADMINISTRATION (SEE TABLE BELOW)

Tegretol suspension in combination with liquid chlorpromazine or thioridazine results in precipitate formation, and, in the case of chlorpromazine, there has been a report of a patient passing an orange rubbery precipitate in the stool following coadministration of the two drugs (see PRECAUTIONS, Drug Interactions). Because the extent to which this occurs with other liquid medications is not known, Tegretol suspension should not be administered simultaneously with other liquid medications or diluents.

Monitoring of blood levels has increased the efficacy and safety of anticonvulsants (see PRECAUTIONS, Laboratory Tests). Dosage should be adjusted to the needs of the individual patient. A low initial daily dosage with a gradual increase is advised. As soon as adequate control is achieved, the dosage may be reduced very gradually to the minimum effective level. Medication should be taken with meals.

Since a given dose of Tegretol suspension will produce higher peak levels than the same dose given as the tablet, it is recommended to start with low doses (children 6 to 12 years: ½ teaspoon four times a day and to increase slowly to avoid unwanted side effects.

Conversion of patients from oral Tegretol tablets to Tegretol suspension: Patients should be converted by administering the same number of mg per day in smaller, more frequent doses (i.e., twice a day tablets to three times a day suspension).

Tegretol-XR is an extended-release formulation for twice a day administration. When converting patients from Tegretol conventional tablets to Tegretol-XR, the same total daily mg dose of Tegretol-XR should be administered. Tegretol-XR tablets must be swallowed whole and never crushed or chewed. Tegretol-XR tablets should be inspected for chips or cracks. Damaged tablets, or tablets without a release portal, should not be consumed. Tegretol-XR tablet coating is not absorbed and is excreted in the feces; these coatings may be noticeable in the stool.

Epilepsy (see INDICATIONS AND USAGE)

Adults and children over 12 years of age-Initial: Either 200 mg twice a day for tablets and XR tablets, or 1 teaspoon four times a day for suspension (400 mg/day). Increase at weekly intervals by adding up to 200 mg/day using a twice a day regimen of Tegretol-XR or a three times a day or four times a day regimen of the other formulations until the optimal response is obtained. Dosage generally should not exceed 1000 mg daily in children 12 to 15 years of age, and 1200 mg daily in patients above 15 years of age. Doses up to 1600 mg daily have been used in adults in rare instances. Maintenance: Adjust dosage to the minimum effective level, usually 800 to 1200 mg daily.

Children 6 to 12 years of age-Initial: Either 100 mg twice a day for tablets or XR tablets, or ½ teaspoon four times a day for suspension (200 mg/day). Increase at weekly intervals by adding up to 100 mg/day using a twice a day regimen of Tegretol-XR or a three times a day or four times a day regimen of the other formulations until the optimal response is obtained. Dosage generally should not exceed 1000 mg daily. Maintenance: Adjust dosage to the minimum effective level, usually 400 to 800 mg daily.

Children under 6 years of age-Initial: 10 to 20 mg/kg/day twice a day or three times a day as tablets, or four times a day as suspension. Increase weekly to achieve optimal clinical response administered three times a day or four times a day. Maintenance: Ordinarily, optimal clinical response is achieved at daily doses below 35 mg/kg. If satisfactory clinical response has not been achieved, plasma levels should be measured to determine whether or not they are in the therapeutic range. No recommendation regarding the safety of carbamazepine for use at doses above 35 mg/kg/24 hours can be made.

Combination Therapy: Tegretol may be used alone or with other anticonvulsants. When added to existing anticonvulsant therapy, the drug should be added gradually while the other anticonvulsants are maintained or gradually decreased, except phenytoin, which may have to be increased (see PRECAUTIONS, Drug Interactions, and Pregnancy).

Trigeminal Neuralgia (see INDICATIONS AND USAGE)

Initial: On the first day, either 100 mg twice a day for tablets or XR tablets, or ½ teaspoon four times a day for suspension, for a total daily dose of 200 mg. This daily dose may be increased by up to 200 mg/day using increments of 100 mg every 12 hours for tablets or XR tablets, or 50 mg (½ teaspoon) four times a day for suspension, only as needed to achieve freedom from pain. Do not exceed 1200 mg daily. Maintenance: Control of pain can be maintained in most patients with 400 to 800 mg daily. However, some patients may be maintained on as little as 200 mg daily, while others may require as much as 1200 mg daily. At least once every 3 months throughout the treatment period, attempts should be made to reduce the dose to the minimum effective level or even to discontinue the drug.

Dosage Information
 | Initial Dose |  |  | Subsequent Dose |  |  | Maximum Daily Dose
Indication | Tablet* | XR† | Suspension | Tablet* | XR† | Suspension | Tablet* | XR† | Suspension
Epilepsy Under 6 yr | 10-20 mg/kg/day twice a day or 3 times a day |  | 10-20 mg/kg/day 4 times a day | Increase weekly to achieve optimal clinical response, 3 times a day or 4 times a day |  | Increase weekly to achieve optimal clinical response, 3 times a day or 4 times a day | 35 mg/kg/24 hr (see Dosage and Administration section above) |  | 35 mg/kg/24 hr (see Dosage and Administration section above)
6-12 yr | 100 mg twice a day (200 mg/day) | 100 mg twice a day (200 mg/day) | ½ tsp 4 times a day (200 mg/day) | Add up to 100 mg/day at weekly intervals, 3 times a day or 4 times a day | Add 100 mg/day at weekly intervals, twice a day | Add up to 1 tsp (100 mg)/day at weekly intervals, 3 times a day or 4 times a day |  | 1000 mg/24 hr
Over 12 yr | 200 mg twice a day (400 mg/day) | 200 mg twice a day (400 mg/day) | 1 tsp 4 times a day (400 mg/day) | Add up to 200 mg/day at weekly intervals, 3 times a day or 4 times a day | Add up to 200 mg/day at weekly intervals, twice a day | Add up to 2 tsp (200 mg)/day at weekly intervals, 3 times a day or 4 times a day | 1000 mg/24 hr (12-15 yr) 1200 mg/24 hr (> 15 yr) 1600 mg/24 hr (adults, in rare instances)
Trigeminal Neuralgia | 100 mg twice a day (200 mg/day) | 100 mg twice a day (200 mg/day) | ½ tsp 4 times a day (200 mg/day) | Add up to 200 mg/day in increments of 100 mg every 12 hr | Add up to 200 mg/day in increments of 100 mg every 12 hr | Add up to 2 tsp (200 mg)/day in increments of 50 mg (½ tsp) 4 times a day |  | 1200 mg/24 hr

*Tablet = conventional tablets.

†XR = Tegretol-XR extended-release tablets.

HOW SUPPLIED

Tablets 200 mg - capsule-shaped, pink, single-scored (imprinted Tegretol on one side and 27 twice on the partially scored side)

Bottles of 100.............................................................................................................................NDC 0078-0509-05

Bottles of 60...............................................................................................................................NDC 0078-0509-20

Store at 20°C to 25°C (68°F to 77°F), excursions permitted between 15°C and 30°C (59°F and 86°F). [See USP Controlled Room Temperature]. Protect from moisture.

Dispense in tight container (USP).

Meets USP Dissolution Test 2.

XR Tablets 100 mg - round, yellow, coated (imprinted “T” on one side and 100 mg on the other), release portal on one side

Bottles of 100.............................................................................................................................NDC 0078-0510-05

XR Tablets 200 mg - round, pink, coated (imprinted “T” on one side and 200 mg on the other), release portal on one side

Bottles of 100.............................................................................................................................NDC 0078-0511-05

XR Tablets 400 mg - round, brown, coated (imprinted “T” on one side and 400 mg on the other), release portal on one side

Bottles of 100.............................................................................................................................NDC 0078-0512-05

Store at 20°C to 25°C (68°F to 77°F), excursions permitted between 15°C and 30°C (59°F and 86°F) [See USP Controlled Room Temperature]. Protect from moisture.

Dispense in tight container (USP).

Suspension 100 mg/5 mL (teaspoon) – yellow-orange, citrus-vanilla flavored

Bottles of 450 mL.......................................................................................................................................NDC 0078-0508-83

Shake well before using.

Do not store above 30°C (86°F). Dispense in tight, light-resistant container (USP).

*Thorazine® is a registered trademark of GlaxoSmithKline.

September 2025
T2025-64

MEDICATION GUIDE

TEGRETOL® and TEGRETOL®-XR (Teg-ret-ol)
(carbamazepine)
Tablets, Suspension, Extended-Release Tablets

Read this Medication Guide before you start taking TEGRETOL or TEGRETOL–XR (TEGRETOL) and each time you get a refill. There may be new information. This information does not take the place of talking to your healthcare provider about your medical condition or treatment.

What is the most important information I should know about TEGRETOL?

Do not stop taking TEGRETOL without first talking to your healthcare provider.

Stopping TEGRETOL suddenly can cause serious problems.

TEGRETOL can cause serious side effects, including:

1. TEGRETOL may cause rare but serious skin rashes that may lead to death. These serious skin reactions are more likely to happen when you begin taking TEGRETOL within the first four months of treatment but may occur at later times. These reactions can happen in anyone, but are more likely in people of Asian descent. If you are of Asian descent, you may need a genetic blood test before you take TEGRETOL to see if you are at a higher risk for serious skin reactions with this medicine. Symptoms may include:
  - skin rash
  - hives
  - sores in your mouth
  - blistering or peeling of the skin
2. TEGRETOL may cause rare but serious blood problems. Symptoms may include:
  - fever, sore throat, or other infections that come and go or do not go away
  - easy bruising
  - red or purple spots on your body
  - bleeding gums or nose bleeds
  - severe fatigue or weakness
3. TEGRETOL may cause allergic reactions or serious problems, which may affect organs and other parts of your body like the liver or blood cells. You may or may not have a rash with these types of reactions.
  Call your healthcare provider right away if you have any of the following:
  - swelling of your face, eyes, lips, or tongue
  - a skin rash
  - painful sores in the mouth or around your eyes
  - unusual bruising or bleeding
  - frequent infections or infections that do not go away
  - fever, swollen glands, or sore throat that do not go away or come and go
  - trouble swallowing or breathing
  - hives
  - yellowing of your skin or eyes
  - severe fatigue or weakness
  - severe muscle pain
4. Tegretol suspension contains 25 mg propylene glycol in each mL. Your healthcare provider will monitor you for side effects of propylene glycol, especially if you are younger than 5 years of age (particularly babies less than 4 weeks old), you have liver or kidney problems, or you are taking other drugs that have propylene glycol or that are broken down by the same enzyme.
5. Like other antiepileptic drugs, TEGRETOL may cause suicidal thoughts or actions in a very small number of people, about 1 in 500.
  Call your healthcare provider right away if you have any of these symptoms, especially if they are new, worse, or worry you:
  - thoughts about suicide or dying
  - attempts to commit suicide
  - new or worse depression
  - new or worse anxiety
  - feeling agitated or restless
  - panic attacks
  - trouble sleeping (insomnia)
  - new or worse irritability
  - acting aggressive, being angry, or violent
  - acting on dangerous impulses
  - an extreme increase in activity and talking (mania)
  - other unusual changes in behavior or mood

How can I watch for early symptoms of suicidal thoughts and actions?

- Pay attention to any changes, especially sudden changes, in mood, behaviors, thoughts, or feelings.
- Keep all follow-up visits with your healthcare provider as scheduled.

Call your healthcare provider between visits as needed, especially if you are worried about symptoms.

Do not stop TEGRETOL without first talking to a healthcare provider.

Stopping TEGRETOL suddenly can cause serious problems. You should talk to your healthcare provider before stopping.

Suicidal thoughts or actions can be caused by things other than medicines. If you have suicidal thoughts or actions, your healthcare provider may check for other causes.

What is TEGRETOL?

TEGRETOL is a prescription medicine used to treat:

- certain types of seizures (partial, tonic-clonic, mixed)
- certain types of nerve pain (trigeminal and glossopharyngeal neuralgia)

TEGRETOL is not a regular pain medicine and should not be used for aches or pains.

Who should not take TEGRETOL?

Do not take TEGRETOL if you:

- have a history of bone marrow depression.
- are allergic to carbamazepine or any of the ingredients in TEGRETOL. See the end of this Medication Guide for a complete list of ingredients in TEGRETOL.
- take nefazodone.
- are allergic to medicines called tricyclic antidepressants (TCAs). Ask your healthcare provider or pharmacist for a list of these medicines if you are not sure.
- have taken a medicine called a Monoamine Oxidase Inhibitor (MAOI) in the last 14 days. Ask your healthcare provider or pharmacist for a list of these medicines if you are not sure.

What should I tell my healthcare provider before taking TEGRETOL?

Before you take TEGRETOL, tell your healthcare provider if you:

- have or have had suicidal thoughts or actions, depression, or mood problems
- have or ever had heart problems
- have or ever had blood problems
- have or ever had liver problems
- have or ever had kidney problems
- have or ever had allergic reactions to medicines
- have or ever had increased pressure in your eye
- have any other medical conditions
- drink grapefruit juice or eat grapefruit
- use birth control. TEGRETOL may make your birth control less effective. Tell your healthcare provider if your menstrual bleeding changes while you take birth control and TEGRETOL.
- are pregnant or plan to become pregnant. TEGRETOL may harm your unborn baby. Tell your healthcare provider right away if you become pregnant while taking TEGRETOL. You and your healthcare provider should decide if you should take TEGRETOL while you are pregnant.
  ▪ If you become pregnant while taking TEGRETOL, talk to your healthcare provider about registering with the North American Antiepileptic Drug (NAAED) Pregnancy Registry. The purpose of this registry is to collect information about the safety of antiepileptic medicine during pregnancy. You can enroll in this registry by calling 1-888-233-2334.
- are breastfeeding or plan to breastfeed. TEGRETOL passes into breast milk. You and your healthcare provider should discuss whether you should take TEGRETOL or breastfeed; you should not do both.

Tell your healthcare provider about all the medicines you take, including prescription and non-prescription medicines, vitamins, and herbal supplements.

Taking TEGRETOL with certain other medicines may cause side effects or affect how well they work. Do not start or stop other medicines without talking to your healthcare provider.

Know the medicines you take. Keep a list of them and show it to your healthcare provider and pharmacist when you get a new medicine.

How should I take TEGRETOL?

- Do not stop taking TEGRETOL without first talking to your healthcare provider. Stopping TEGRETOL suddenly can cause serious problems. Stopping seizure medicine suddenly in a patient who has epilepsy may cause seizures that will not stop (status epilepticus).
- Take TEGRETOL exactly as prescribed. Your healthcare provider will tell you how much TEGRETOL to take.
- Your healthcare provider may change your dose. Do not change your dose of TEGRETOL without talking to your healthcare provider.
- Take TEGRETOL with food.
- TEGRETOL-XR Tablets:
  - Do not crush, chew, or break TEGRETOL-XR tablets.
  - Tell your healthcare provider if you cannot swallow TEGRETOL-XR whole.
- TEGRETOL Suspension:
  - Shake the bottle well each time before use.
  - Do not take TEGRETOL suspension at the same time you take other liquid medicines.
- If you take too much TEGRETOL, call your healthcare provider or local Poison Control Center right away.

What should I avoid while taking TEGRETOL?

- Do not drink alcohol or take other drugs that make you sleepy or dizzy while taking TEGRETOL until you talk to your healthcare provider. TEGRETOL taken with alcohol or drugs that cause sleepiness or dizziness may make your sleepiness or dizziness worse.
- Do not drive, operate heavy machinery, or do other dangerous activities until you know how TEGRETOL affects you. TEGRETOL may slow your thinking and motor skills.

What are the possible side effects of TEGRETOL?

See “What is the most important information I should know about TEGRETOL?”

TEGRETOL may cause other serious side effects. These include:

- Irregular heartbeat - symptoms include:
  - Fast, slow, or pounding heartbeat
  - Shortness of breath
  - Feeling lightheaded
  - Fainting

- Liver problems - symptoms include:
  - yellowing of your skin or the whites of your eyes
  - dark urine
  - pain on the right side of your stomach area (abdominal pain)
  - easy bruising
  - loss of appetite
  - nausea or vomiting

Get medical help right away if you have any of the symptoms listed above or listed in “What is the most important information I should know about TEGRETOL?”

The most common side effects of TEGRETOL include:

- dizziness
- drowsiness
- problems with walking and coordination (unsteadiness)
- nausea
- vomiting

These are not all the possible side effects of TEGRETOL. For more information, ask your healthcare provider or pharmacist.

Tell your healthcare provider if you have any side effect that bothers you or that does not go away.

Call your doctor for medical advice about side effects. You may report side effects to FDA at 1-800-FDA-1088.

How should I store TEGRETOL?

- Store TEGRETOL Tablets at 20°C to 25°C (68°F to 77°F), excursions permitted between 15°C and 30°C (59°F and 86°F).
  - Keep TEGRETOL Tablets dry.
- Store TEGRETOL-XR Tablets at 20°C to 25°C (68°F to 77°F); excursions permitted between 15°C and 30°C (59°F and 86°F).
  - Keep TEGRETOL-XR Tablets dry.
- Do not store TEGRETOL Suspension above 30°C (86°F).
  - Shake well before using.
  - Keep TEGRETOL Suspension in a tight, light-resistant container.

Keep TEGRETOL and all medicines out of the reach of children.

General Information about TEGRETOL.

Medicines are sometimes prescribed for purposes other than those listed in a Medication Guide. Do not use TEGRETOL for a condition for which it was not prescribed. Do not give TEGRETOL to other people, even if they have the same symptoms that you have. It may harm them.

This Medication Guide summarizes the most important information about TEGRETOL. If you would like more information, talk with your healthcare provider. You can ask your pharmacist or healthcare provider for the full prescribing information about TEGRETOL that is written for health professionals.

For more information, go to www.novartis.us or call 1-888-669-6682.

What are the ingredients in TEGRETOL?

Active ingredient: carbamazepine

Inactive ingredients:

- TEGRETOL Tablets: colloidal silicon dioxide, FD&C Red No. 40, gelatin, glycerin, magnesium stearate, starch, and stearic acid.
- TEGRETOL Suspension: citric acid, FD&C Yellow No. 6, flavoring, polymer, potassium sorbate, propylene glycol (25 mg/ mL), purified water, sorbitol, sucrose, and xanthan gum.
- TEGRETOL-XR Tablets: cellulose compounds, dextrates, iron oxides, magnesium stearate, mannitol, polyethylene glycol, sodium lauryl sulfate, titanium dioxide (200 mg tablets only).

This Medication Guide has been approved by the U.S. Food and Drug Administration.

Distributed by:
Novartis Pharmaceuticals Corporation
East Hanover, New Jersey 07936

© Novartis

September 2025
T2025-65

PRINCIPAL DISPLAY PANEL

NDC 0078-0509-05

Rx only

Tegretol® 200 mg

carbamazepine USP

100 tablets

PHARMACIST: Dispense with Medication Guide
attached or provided separately.

NOVARTIS

PRINCIPAL DISPLAY PANEL

NDC 0078-0510-05

Rx only

Tegretol®-XR 100 mg

(carbamazepine extended-release tablets)

Tegretol-XR tablets must be swallowed
whole and never crushed or chewed.

100 tablets

PHARMACIST: Dispense with Medication Guide
attached or provided separately.

NOVARTIS

PRINCIPAL DISPLAY PANEL

NDC 0078-0511-05

Rx only

Tegretol®-XR 200 mg

(carbamazepine extended-release tablets)

Tegretol-XR tablets must be swallowed
whole and never crushed or chewed.

100 tablets

PHARMACIST: Dispense with Medication Guide
attached or provided separately.

NOVARTIS

PRINCIPAL DISPLAY PANEL

NDC 0078-0512-05

Rx only

Tegretol®-XR 400 mg

(carbamazepine extended-release tablets)

Tegretol-XR tablets must be swallowed
whole and never crushed or chewed.

100 tablets

PHARMACIST: Dispense with Medication Guide
attached or provided separately.

NOVARTIS

PRINCIPAL DISPLAY PANEL

NDC 0078-0508-83

Tegretol®
(carbamazepine USP)
Suspension

100 mg/5 mL

IMPORTANT: Shake well before using.

Each 5 mL contains 100 mg carbamazepine USP.

450 mL

Dispense in tight, light-resistant
container (USP).

PHARMACIST: Dispense with
Medication Guide attached or
provided separately.

Rx only

NOVARTIS